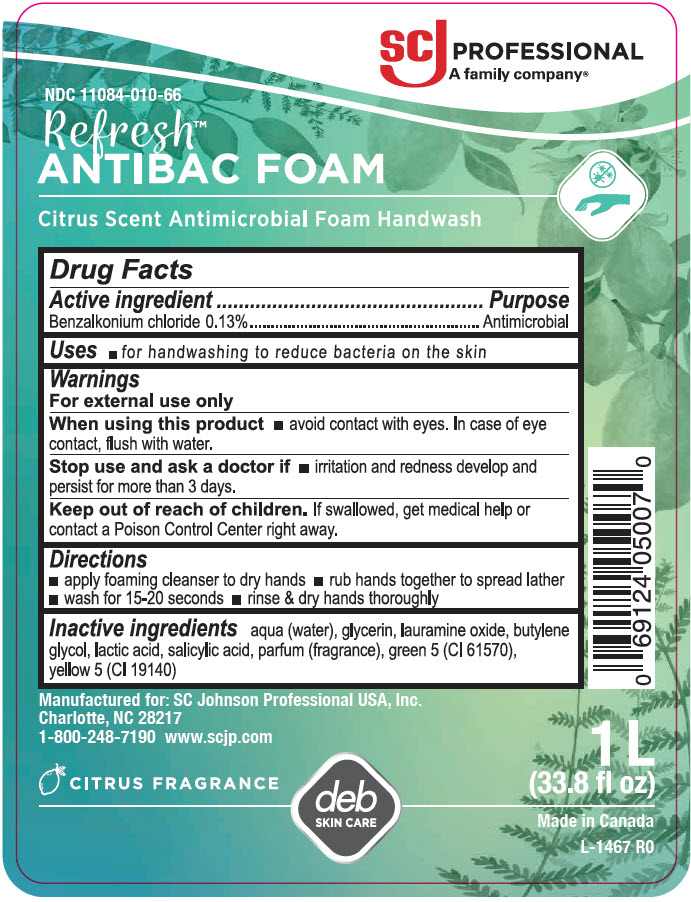 DRUG LABEL: Refresh AntiBac FOAM
NDC: 11084-010 | Form: SOAP
Manufacturer: SC Johnson Professional USA Inc.
Category: otc | Type: HUMAN OTC DRUG LABEL
Date: 20251223

ACTIVE INGREDIENTS: BENZALKONIUM CHLORIDE 0.13 g/1 L
INACTIVE INGREDIENTS: WATER; GLYCERIN; LAURAMINE OXIDE; BUTYLENE GLYCOL; LACTIC ACID, UNSPECIFIED FORM; SALICYLIC ACID; D&C GREEN NO. 5; FD&C YELLOW NO. 5

Drug Facts

Active ingredient

BENZALKONIUM CHLORIDE, 0.13%

Purpose

Antimicrobial

Uses

for handwashing to reduce bacteria on the skin

Warnings

When using this product

avoid contact with eyes. In case of eye contact, flush with water.

Stop use and ask a doctor if

irritation and redness develop and persist for more than 3 days.

Keep out of reach of children.

If swallowed, get medical help or contact a Poison Control Center right away.

Directions

apply foaming cleanser to dry hands
rub hands together to spread lather
wash for 15-20 seconds
rinse & dry hands thoroughly

Inactive ingredients

AQUA (WATER), GLYCERIN, LAURAMINE OXIDE, BUTYLENE GLYCOL, LACTIC ACID, SALICYLIC ACID, PARFUM (FRAGRANCE), GREEN 5 (CI 61570), YELLOW 5 (CI 19140).

PRINCIPAL DISPLAY PANEL - 1 L Bottle Label

SCJ Professional
A family company®

NDC 11084-010-66

Refresh™

ANTIBAC FOAM

Citrus Scent Antimicrobial Foam Handwash

Manufactured for: SC Johnson Professional USA, Inc.
Charlotte, NC 28217
1-800-248-7190 www.scjp.com

CITRUS FRAGRANCE

deb
SKIN CARE

1 L
(33.8 fl oz)

Made in Canada
L-1467 R0